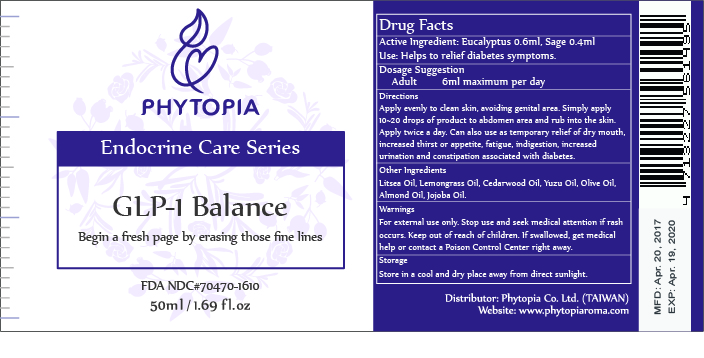 DRUG LABEL: GLP-1 Balance
NDC: 70470-1610 | Form: OIL
Manufacturer: Phytopia Co., Ltd.
Category: otc | Type: HUMAN OTC DRUG LABEL
Date: 20200514

ACTIVE INGREDIENTS: EUCALYPTUS OIL 60 mg/50 mL; SAGE OIL 40 mg/50 mL
INACTIVE INGREDIENTS: ALMOND OIL; CITRUS MAXIMA FRUIT RIND OIL; JOJOBA OIL; OLIVE OIL; LITSEA OIL; WEST INDIAN LEMONGRASS OIL; CEDRUS ATLANTICA BARK OIL

Drug Facts

Eucalyptus Oil 0.6ml

Sage Oil 0.4ml

Use

Helps to relief diabetes symptoms.

Dosage Suggestion

Adult 6ml maximum per day

Directions

Apply evenly to clean skin, avoiding genital area. Simply apply 10~20 drops of product to abdomen area and rub into the skin. Apply twice a day. Can also use as temporary relief of dry mouth, increased thirst or appetite, fatigue, indigestion, increased urination and constipation associated with diabetes.

INACTIVE INGREDIENT

Other Ingredients

Litsea Oil, Lemongrass Oil, Cedarwood Oil, Yuzu Oil, Olive Oil, Almond Oil, Jojoba Oil.

Warnings

For external use only. Stop use and ask doctor if rash occurs. Keep out reach of children.

Other Information

Protect this product from excessive heat

and direct sun.

Warnings

For external use only. Stop use and ask doctor if rash occurs. Keep out reach of children.